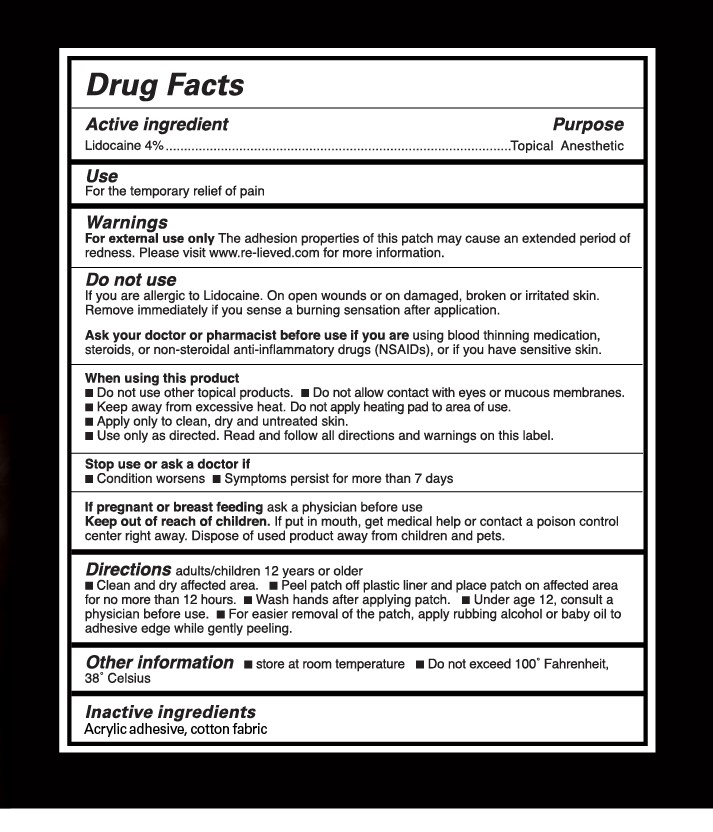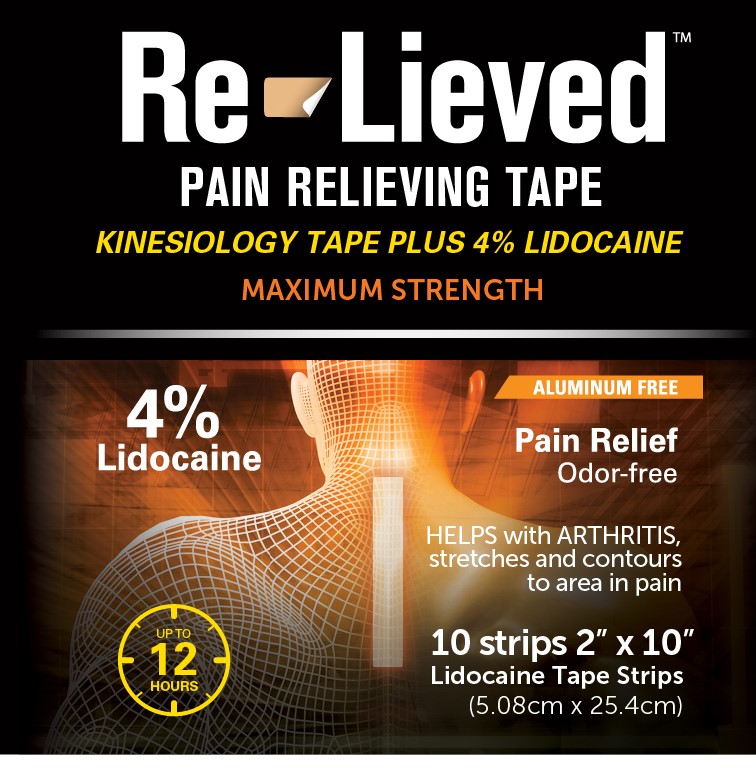 DRUG LABEL: Re-Lieved 4% Lidocaine Fabric Tape
NDC: 71662-002 | Form: PATCH
Manufacturer: Transfer Technology
Category: otc | Type: HUMAN OTC DRUG LABEL
Date: 20250111

ACTIVE INGREDIENTS: LIDOCAINE 18 mg/116 cm2
INACTIVE INGREDIENTS: ACRYLIC ACID/ETHYLENE COPOLYMER (600 MPA.S)

Re-Lieved Lidocaine 4% Fabric Tape

Active Ingredient

Lidocaine 4%

Purpose

Topical Analgesic

Use

For the temporary relief of pain

Warnings

For external use only

Do not use

If you are allergic to Lidocaine. On open wounds or on damaged broken or irritated skin

Remove immediately if you sense a burning sensation after application

Ask your doctor or pharmacist before use if you are using blood thining medication, steroids, or non-steroidal anti-inflammatory drugs (NSAIDS), or if you have sensitive skin.

When using this product

- do not use other topical products
- Do not allow contact with eyes or mucous membranes
- Keep away from excessive heat. Do not apply heating pad to areea of use
- Apply only to clean, dry, and untreated skin.
- Use only as directed. Read and follow all directions and warnings on this label

Stop use or ask a doctor if

- Condition worsens
- Symptons persist for more than 7 days

PREGNANCY

If pregnant or breastfeeding ask a physican before use.

Keep out of reach of children. If put in mouth, get medical help or contact a poison control center right away. Dispose of used product away from children and pets.

Keep out of reach of children. If put in mouth, get medical help or contact a poison control center right away.

DOSAGE AND ADMINISTRATION

Directions adults and children 12 years or older

- Peel patch off plastic liner and place patch over affected area.
- Change patch 1 to 2 times a day.
- Wash hands after applying patch
- Under age 12 consult a physician before use

Other information

- Store at room temperature
- Do not exceed 100o Fahrenheit 38o Celsius
- For easier removal of patch apply rubbing alcohol or baby oil to adhesive edge

Inactive ingredients: Acrylic adhesive, polyethylene foam

Other information

- store at room tempertaure
- Do not exceed 100o Fahrenheit, 38o Celsius